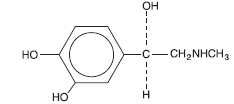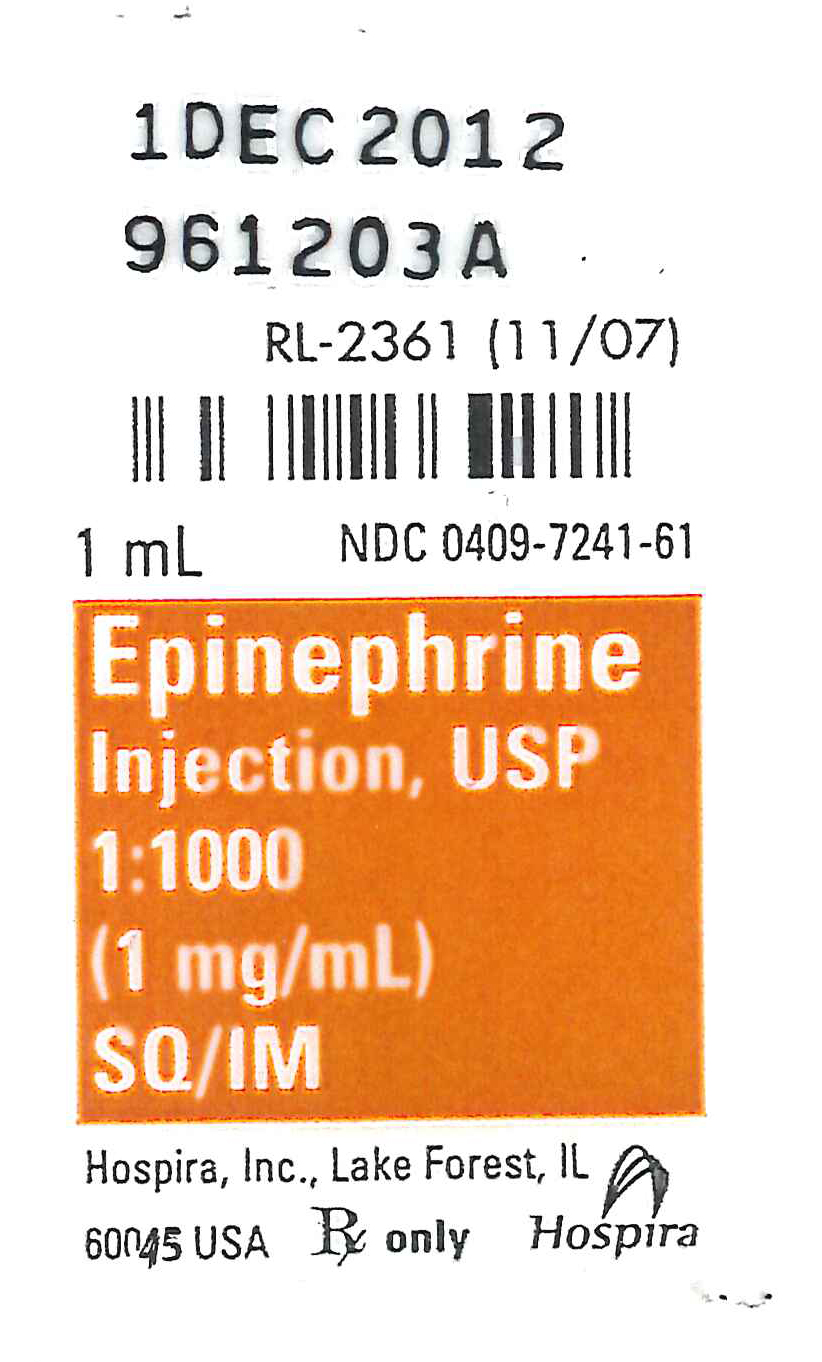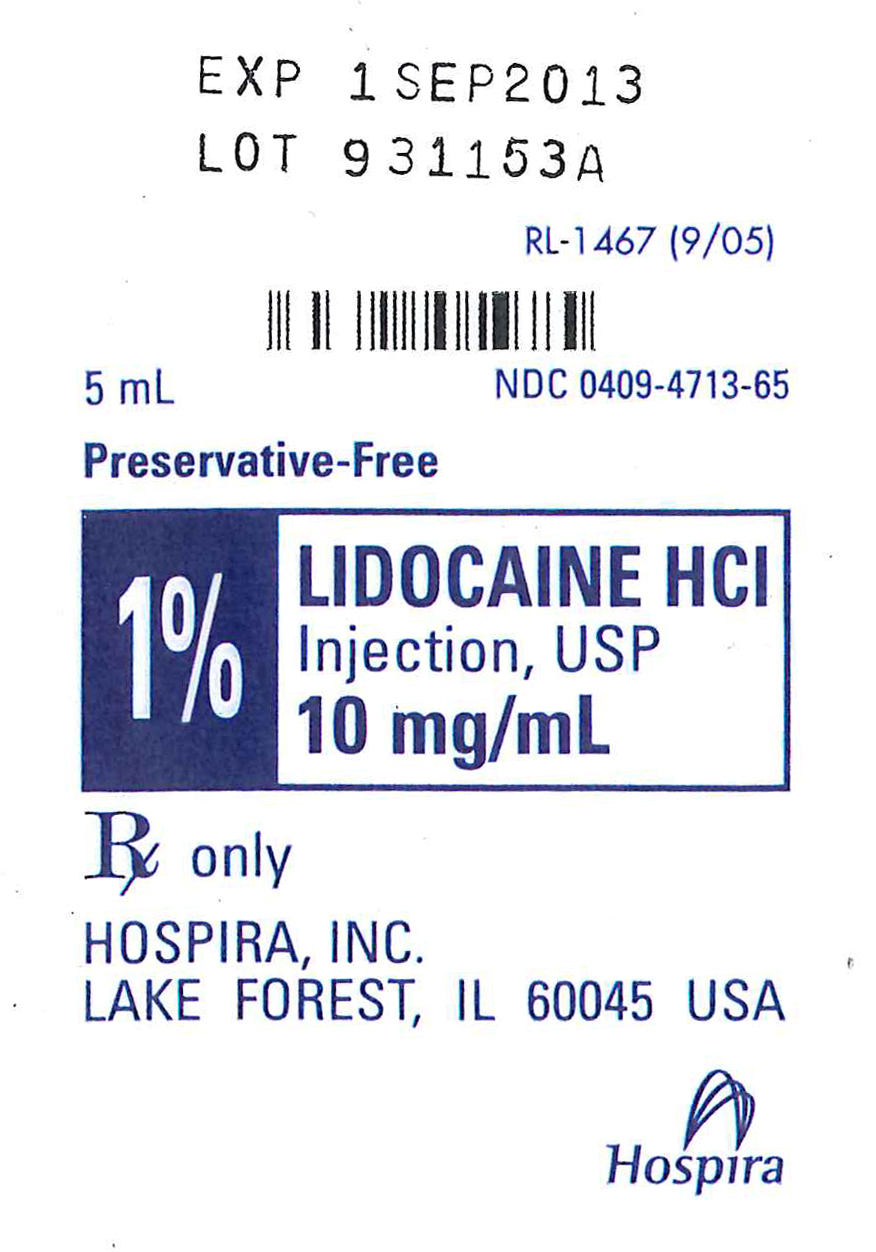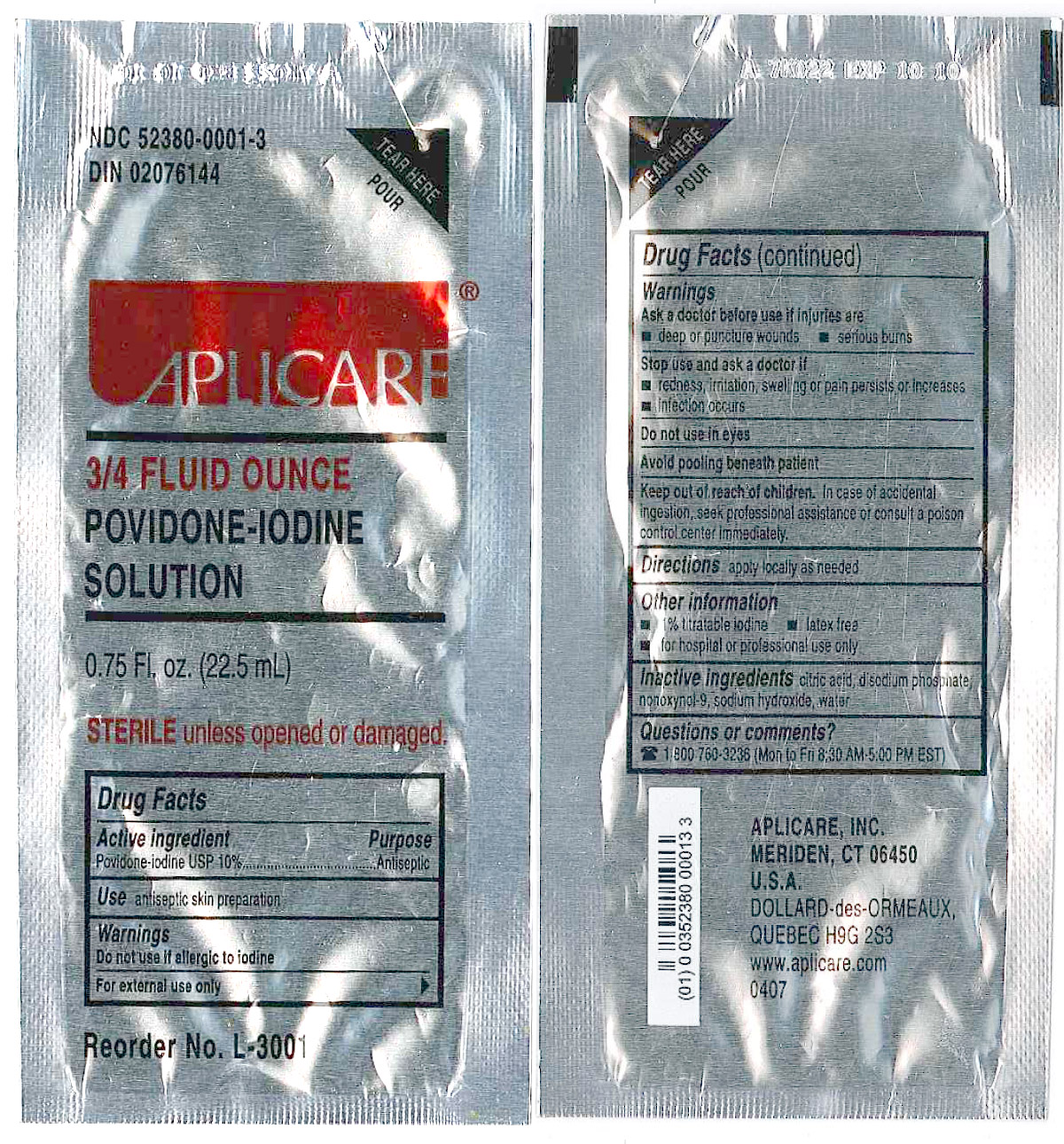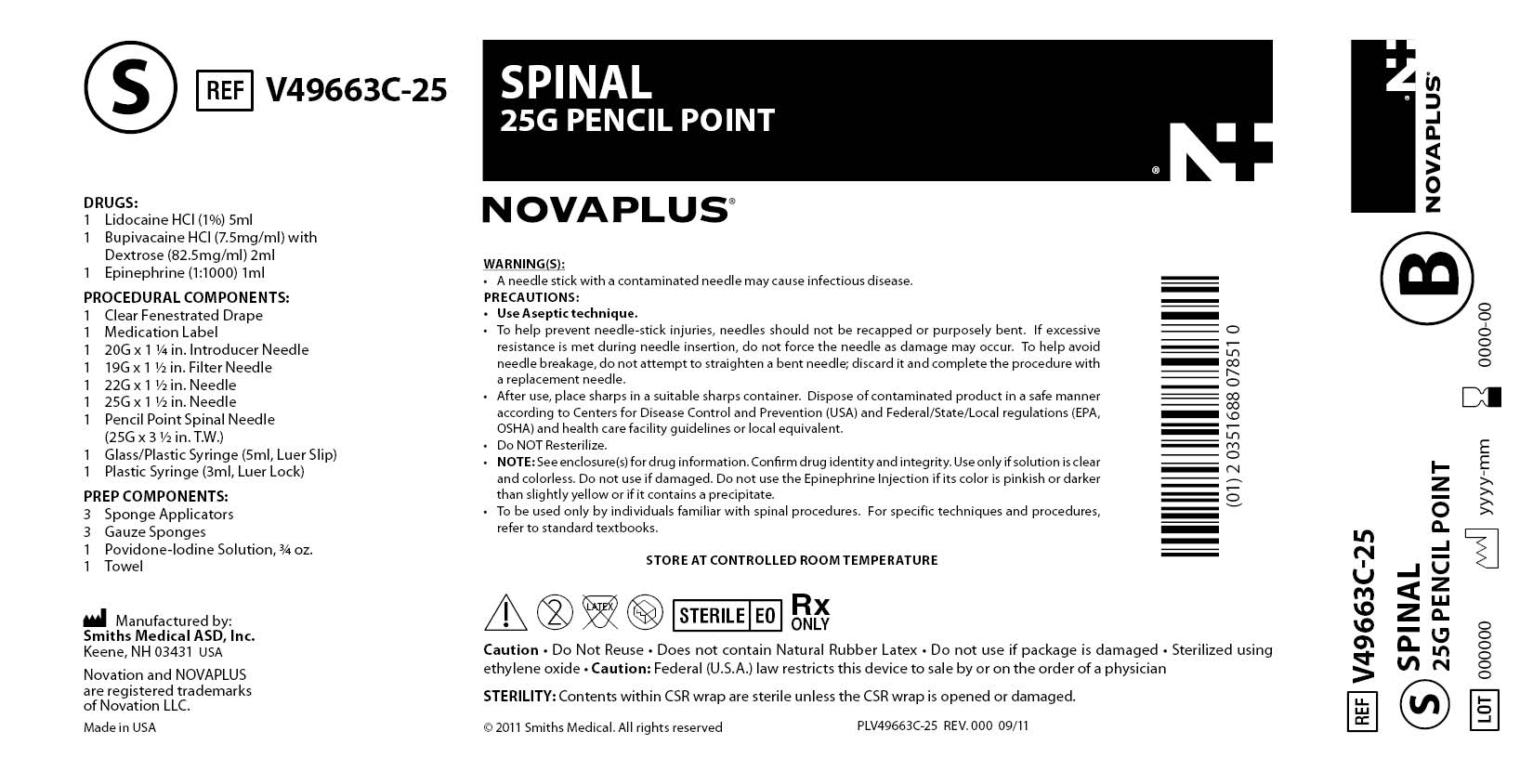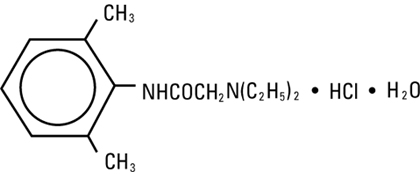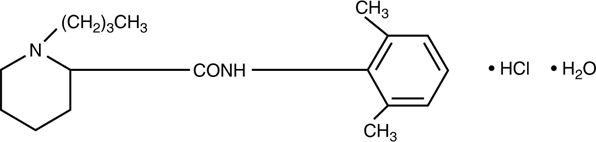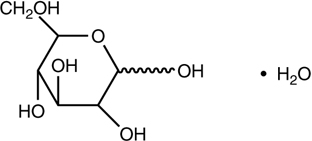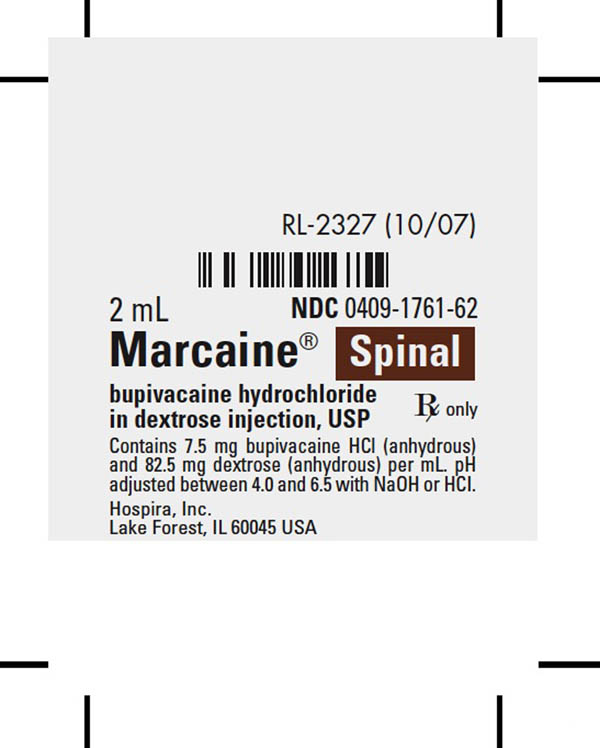 DRUG LABEL: V49663C-25 SPINAL 25G PENCIL POINT NOVAPLUS
NDC: 51688-6264 | Form: C47916 | Route: INTRATHECAL
Manufacturer: Smiths Medical ASD, Inc.
Category: other | Type: MEDICAL DEVICE
Date: 20200318

ACTIVE INGREDIENTS: EPINEPHRINE 1 mg/1 mL; LIDOCAINE HYDROCHLORIDE 10 mg/1 mL; POVIDONE-IODINE 10 mg/1 mL; BUPIVACAINE HYDROCHLORIDE 7.5 mg/1 mL
INACTIVE INGREDIENTS: SODIUM CHLORIDE 9 mg/1 mL; SODIUM METABISULFITE 0.9 mg/1 mL; Sodium Chloride 7 mg/1 mL; Water; Sodium Hydroxide; Hydrochloric Acid; CITRIC ACID MONOHYDRATE; SODIUM PHOSPHATE, DIBASIC; SODIUM HYDROXIDE; NONOXYNOL-9; WATER; ANHYDROUS DEXTROSE 82.5 mg/1 mL; SODIUM HYDROXIDE; HYDROCHLORIC ACID

DESCRIPTION

EPINEPHRINE injection, USP

1:1000 (1 mg/mL)

Ampul
Protect from light until ready to use.

Rx only

Description

Epinephrine Injection, USP 1:1000 is a sterile, nonpyrogenic solution. Each mL contains epinephrine 1 mg; sodium chloride 9 mg; sodium metabisulfite 0.9 mg added. May contain
hydrochloric acid for pH adjustment. The solution contains no bacteriostat or antimicrobial agent. It is administered by the following routes: intravenous, intracardiac (left ventricular chamber), via endotracheal tube into the bronchial tree, subcutaneous or intramuscular. Epinephrine, USP is a sympathomimetic (adrenergic) agent designated chemically as 4-[1-hydroxy-2 (methylamino) ethyl]-1,2 benzenediol, a white, microcrystalline powder. It has the following structural formula:

Sodium Chloride, USP is chemically designated NaCl, a white, crystalline compound freely soluble in water.

Clinical Pharmacology

The actions of epinephrine resemble the effects of stimulation of adrenergic nerves. To a variable degree it acts on both alpha and beta receptor sites of sympathetic effector cells. Its most prominent actions are on the beta receptors of the heart, vascular and other smooth muscle. When given by rapid intravenous injection, it produces a rapid rise in blood pressure, mainly systolic, by (1) direct stimulation of cardiac muscle which increases the strength of ventricular contraction, (2) increasing the heart rate and (3) constriction of the arterioles in the skin, mucosa and splanchnic areas of the circulation. When given by slow intravenous injection epinephrine usually produces only a moderate rise in systolic and a fall in diastolic pressure. Although some increase in pulse pressure occurs, there is usually no great elevation in mean blood pressure. Accordingly, the compensatory reflex mechanisms that come into play with a pronounced increase in blood pressure do not antagonize the direct cardiac actions of epinephrine as much as with catecholamines that have a predominant action on alpha receptors.
Total peripheral resistance decreases by action of epinephrine on beta receptors of the skeletal muscle vasculature and blood flow is thereby enhanced. Usually this vasodilator effect of the drug on the circulation predominates so that the modest rise in systolic pressure which follows slow injection or absorption is mainly the result of direct cardiac stimulation and increase in cardiac output. In some instances peripheral resistance is not altered or may even rise owing to a greater ratio of alpha to beta activity in different vascular areas. Epinephrine relaxes the smooth muscles of the bronchi and iris and is a physiologic antagonist of histamine. The drug also produces an increase in blood sugar and glycogenolysis in the liver. Intravenous injection produces an immediate and intensified response. Following intravenous injection epinephrine disappears rapidly from the blood stream. Epinephrine is rapidly inactivated in the body and is degraded by enzymes in the liver and other tissues. The large portion of injection doses is excreted in the urine as inactivated compounds. The remainder is excreted in the urine as unchanged or conjugated compounds.

Indications and Usage

Epinephrine is used to relieve respiratory distress due to bronchospasm, to provide rapid relief of hypersensitivity reactions to drugs and other allergens, and to prolong the action of anesthetics. Its cardiac effects may be of use in restoring cardiac rhythm in cardiac arrest due to various causes, but it is not used in cardiac failure or in hemorrhagic, traumatic, or cardiogenic shock. Epinephrine is used as a hemostatic agent. It is also used in treating mucosal congestion of hay fever, rhinitis, and acute sinusitis; to relieve bronchial asthmatic paroxysms; in syncope due to complete heart block or carotid sinus hypersensitivity; for symptomatic relief of serum sickness, urticaria, angioneurotic edema; for resuscitation in cardiac arrest following anesthetic accidents; in simple (open angle) glaucoma; for relaxation of uterine musculature and to inhibit uterine contractions. Epinephrine Injection can be utilized to prolong the action of anesthetics used in local and regional anesthesia.

Contraindications

Epinephrine is contraindicated in patients with known hypersensitivity to sympathomimetic amines, in patients with angle closure glaucoma, and patients in shock (nonanaphylactic). It should
not be used in patients anesthetized with agents such as cyclopropane or halothane as these may sensitize the heart to the arrhythmic action of sympathomimetic drugs. Addition of epinephrine to local anesthetics for injection of certain areas (e.g., fingers, toes, ears, etc.) is contraindicated because of danger that vasoconstriction may result in sloughing of tissue.
Except as diluted for admixture with local anesthetics to reduce absorption and prolong action, epinephrine should not ordinarily be used in those cases where vasopressor drugs may be
contraindicated, e.g., in thyrotoxicosis, diabetes, in obstetrics when maternal blood pressure is in excess of 130/80 and in hypertension and other cardiovascular disorders.

Warnings

Inadvertently induced high arterial blood pressure may result in angina pectoris, aortic rupture or cerebral hemorrhage. Epinephrine may induce potentially serious cardiac arrhythmias in patients not suffering from heart disease and in patients with organic heart disease or who are receiving drugs that sensitize the myocardium. Parenterally administered epinephrine initially may produce constriction of renal blood vessels and decrease urine formation. Epinephrine Injection, USP is subject to oxidation and should be protected against exposure to light and stored in light-resistant containers. Epinephrine is the preferred treatment for serious allergic or other emergency situations even though this product contains sodium metabisulfite, a sulfite that may in other products cause allergic-type reactions including anaphylactic symptoms or life-threatening or less severe asthmatic episodes in certain susceptible persons. The alternatives to using epinephrine in a life-threatening situation may not be satisfactory. The presence of a sulfite in this product should not deter administration of the drug for treatment of serious allergic or other emergency situations.

Precautions

Do not use the Injection if its color is pinkish or darker than slightly yellow or if it contains a precipitate. Do not administer unless solution is clear and container is intact. Discard unused portion. Although epinephrine can produce ventricular fibrillation, its actions in restoring electrical activity in asystole and in enhancing defibrillation of the fibrillating ventricle are well documented. The drug, however, should be used with caution in patients with ventricular fibrillation. Epinephrine should be used cautiously in patients with hyperthyroidism, hypertension and
cardiac arrhythmias. All vasopressors should be used cautiously in patients taking monoamine oxidase (MAO) inhibitors. Epinephrine should not be administered concomitantly with other sympathomimetic drugs (such as isoproterenol) because of possible additive effects and increased toxicity. Combined effects may induce serious cardiac arrhythmias. They may be administered alternately when the preceding effect of other such drugs has subsided. Administration of epinephrine to patients receiving cyclopropane or halogenated hydrocarbon general anesthetics such as halothane which sensitize the myocardium, may induce cardiac arrhythmia. (See CONTRAINDICATIONS.) When encountered, such arrhythmias may respond to administration of a beta-adrenergic blocking drug. Epinephrine also should be used cautiously with other drugs (e.g., digitalis glycosides) that sensitize the myocardium to the actions of
sympathomimetic agents. Diuretic agents may decrease vascular response to pressor drugs such as epinephrine. Epinephrine may antagonize the neuron blockade produced by guanethidine resulting in decreased antihypertensive effect and requiring increased dosage of the latter.

Pregnancy Category C. Animal reproduction studies have not been conducted with epinephrine. It is also not known whether epinephrine can cause fetal harm when administered to a
pregnant woman or can affect reproduction capacity. Epinephrine should be given to a pregnant woman only if clearly needed.

Labor and Delivery. Parenteral administration of epinephrine if used to support blood pressure during low or other spinal anesthesia for delivery can cause acceleration of fetal heart rate and
should not be used in obstetrics when maternal blood pressure exceeds 130/80. (See CONTRAINDICATIONS.)

Adverse Reactions

Transient and minor side effects of anxiety, headache, fear and palpitations occur only with systemic therapeutic doses, especially in hyperthyroid individuals. Adverse effects such as cardiac arrhythmias and excessive rise in blood pressure may occur with systemic therapeutic doses or with inadvertent overdosage. Other adverse reactions include cerebral hemorrhage, hemiplegia, subarachnoid hemorrhage, anginal pain in patients with angina pectoris, anxiety, restlessness, headache, tremor, weakness, dizziness, pallor and respiratory difficulty. Such reactions are unlikely when epinephrine is diluted to 1:200,000 for injection with local anesthetic agents.

Overdosage

Erroneous administration of large doses of epinephrine may lead to precordial distress, vomiting, headache, dyspnea, as well as unusually elevated blood pressure. (See WARNINGS.) Toxic effects of overdosage can be counteracted by injection of an alpha-adrenergic blocker and a betaadrenergic blocker. In the event of a sharp rise in blood pressure, rapid-acting vasodilators such as the nitrites, or alpha-adrenergic blocking agents can be given to counteract the marked pressor effect of large doses of epinephrine.

Dosage and Administration

Subcutaneously or intramuscularly – 0.2 to 1 mL (mg). Start with a small dose and increase if required.
Note: The subcutaneous is the preferred route of administration. If given intramuscularly, injection into the buttocks should be avoided.

Hypersensitivity Reactions
For bronchial asthma and certain allergic manifestations, e.g., angioedema, urticaria, serum sickness, anaphylactic shock, use epinephrine subcutaneously. The adult intravenous dose for
hypersensitivity reactions or to relieve bronchospasm usually ranges from 0.1 to 0.25 mg injected slowly. Neonates may be given a dose of 0.01 mg per kg of body weight; for the infant 0.05 mg is an adequate initial dose and this may be repeated at 20 to 30 minute intervals in the management of asthma attacks.
Cardiac Resuscitation
A dose of 0.5 mL (0.5 mg) diluted to 10 mL with sodium chloride injection can be administered intravenously or intracardially to restore myocardial contractility. Intracardiac injection should only be administered by personnel well trained in the technique, if there has not been sufficient time to establish an intravenous route. External cardiac massage should follow intracardial administration to permit the drug to enter coronary circulation. The drug should be used secondarily to unsuccessful attempts with physical or electromechanical methods.
Ophthalmologic Use
Ophthalmologic use (for producing conjunctival decongestion, to control hemorrhage, produce mydriasis and reduce intraocular pressure) – use a concentration of 1:10,000 (0.1 mg/mL) to
1:1000 (1 mg/mL).
Regional Anesthesia
A final concentration of 1:200,000 of epinephrine injection is recommended for infiltration injection, nerve block, caudal or other epidural blocks. From 0.3 to 0.4 mg of epinephrine (0.3 to
0.4 mL of 1:1000 solution) may be mixed with spinal anesthetic agents. Parenteral drug products should be inspected visually for particulate matter and discoloration prior to administration. (See PRECAUTIONS.)

HOW SUPPLIED

<paragraph>How SuppliedEpinephrine Injection, USP 1:1000 (1 mg/mL) is supplied in a 1 mL ampul single-dose container (NDC 0409-7241-61).
Store at 20 to 25°C (68 to 77°F). [See USP Controlled Room Temperature.]
Protect from light.
Revised: October, 2008
Printed in USA EN-1927
Hospira, Inc., Lake Forest, IL 60045 USA

DESCRIPTION

LIDOCAINE HYDROCHLORIDE (lidocaine hydrochloride anhydrous) injection, solution

AQUEOUS SOLUTIONS FOR INFILTRATION

AND NERVE BLOCK

Ampul

Plastic Multiple-dose Fliptop Vial

Glass Teartop Vial

Rx only

DESCRIPTION

Lidocaine Hydrochloride Injection, USP is a sterile, nonpyrogenic solution of lidocaine hydrochloride in water for injection for parenteral administration in various concentrations with characteristics as follows:

Concentration | 0.5% | 1% | 1.5% | 2%
mg/mL lidocaine HCl (anhyd.) | 5 | 10 | 15 | 20
mg/mL sodium chloride | 8 | 7 | 6.5 | 6

Multiple-dose vials contain 0.1% of methylparaben added as preservative. May contain sodium hydroxide and/or hydrochloric acid for pH adjustment. The pH is 6.5 (5.0 to 7.0). See HOW SUPPLIED section for various sizes and strengths.

Lidocaine is a local anesthetic of the amide type.

Lidocaine Hydrochloride, USP is chemically designated 2-(diethylamino)-N-(2,6-dimethylphenyl)-acetamide monohydrochloride monohydrate, a white powder freely soluble in water. The molecular weight is 288.82. It has the following structural formula:

The semi-rigid vial used for the plastic vials is fabricated from a specially formulated polyolefin. It is a copolymer of ethylene and propylene. The safety of the plastic has been confirmed by tests in animals according to USP biological standards for plastic containers. The container requires no vapor barrier to maintain the proper drug concentration.

CLINICAL PHARMACOLOGY

Mechanism of action: Lidocaine stabilizes the neuronal membrane by inhibiting the ionic fluxes required for the initiation and conduction of impulses, thereby effecting local anesthetic action.

Hemodynamics: Excessive blood levels may cause changes in cardiac output, total peripheral resistance, and mean arterial pressure. With central neural blockade these changes may be attributable to block of autonomic fibers, a direct depressant effect of the local anesthetic agent on various components of the cardiovascular system and/or the beta-adrenergic receptor stimulating action of epinephrine when present. The net effect is normally a modest hypotension when the recommended dosages are not exceeded.

Pharmacokinetics and metabolism: Information derived from diverse formulations, concentrations and usages reveals that lidocaine is completely absorbed following parenteral administration, its rate of absorption depending, for example, upon various factors such as the site of administration and the presence or absence of a vasoconstrictor agent. Except for intravascular administration, the highest blood levels are obtained following intercostal nerve block and the lowest after subcutaneous administration.

The plasma binding of lidocaine is dependent on drug concentration, and the fraction bound decreases with increasing concentration. At concentrations of 1 to 4 mcg of free base per mL, 60 to 80 percent of lidocaine is protein bound. Binding is also dependent on the plasma concentration of the alpha-1-acid glycoprotein.

Lidocaine crosses the blood-brain and placental barriers, presumably by passive diffusion.

Lidocaine is metabolized rapidly by the liver, and metabolites and unchanged drug are excreted by the kidneys. Biotransformation includes oxidative N-dealkylation, ring hydroxylation, cleavage of the amide linkage, and conjugation. N-dealkylation, a major pathway of biotransformation, yields the metabolites monoethylglycinexylidide and glycinexylidide. The pharmacological/toxicological actions of these metabolites are similar to, but less potent than, those of lidocaine. Approximately 90% of lidocaine administered is excreted in the form of various metabolites, and less than 10% is excreted unchanged. The primary metabolite in urine is a conjugate of 4-hydroxy-2, 6-dimethylaniline.

The elimination half-life of lidocaine following an intravenous bolus injection is typically 1.5 to 2.0 hours. Because of the rapid rate at which lidocaine is metabolized, any condition that affects liver function may alter lidocaine kinetics. The half-life may be prolonged two-fold or more in patients with liver dysfunction. Renal dysfunction does not affect lidocaine kinetics but may increase the accumulation of metabolites.

Factors such as acidosis and the use of CNS stimulants and depressants affect the CNS levels of lidocaine required to produce overt systemic effects. Objective adverse manifestations become increasingly apparent with increasing venous plasma levels above 6.0 mcg free base per mL. In the rhesus monkey arterial blood levels of 18-21 mcg/mL have been shown to be threshold for convulsive activity.

INDICATIONS AND USAGE

Lidocaine Hydrochloride Injection, USP is indicated for production of local or regional anesthesia by infiltration techniques such as percutaneous injection and intravenous regional anesthesia by peripheral nerve block techniques such as brachial plexus and intercostal and by central neural techniques such as lumbar and caudal epidural blocks, when the accepted procedures for these techniques as described in standard textbooks are observed.

CONTRAINDICATIONS

Lidocaine is contraindicated in patients with a known history of hypersensitivity to local anesthetics of the amide type.

WARNINGS

LIDOCAINE HYDROCHLORIDE INJECTION, FOR INFILTRATION AND NERVE BLOCK, SHOULD BE EMPLOYED ONLY BY CLINICIANS WHO ARE WELL VERSED IN DIAGNOSIS AND MANAGEMENT OF DOSE-RELATED TOXICITY AND OTHER ACUTE EMERGENCIES THAT MIGHT ARISE FROM THE BLOCK TO BE EMPLOYED AND THEN ONLY AFTER ENSURING THE IMMEDIATE AVAILABILITY OF OXYGEN, OTHER RESUSCITATIVE DRUGS, CARDIOPULMONARY EQUIPMENT, AND THE PERSONNEL NEEDED FOR PROPER MANAGEMENT OF TOXIC REACTIONS AND RELATED EMERGENCIES (See also ADVERSE REACTIONS and PRECAUTIONS). DELAY IN PROPER MANAGEMENT OF DOSE-RELATED TOXICITY, UNDERVENTILATION FROM ANY CAUSE AND/OR ALTERED SENSITIVITY MAY LEAD TO THE DEVELOPMENT OF ACIDOSIS, CARDIAC ARREST AND, POSSIBLY, DEATH.

Intra-articular infusions of local anesthetics following arthroscopic and other surgical procedures is an unapproved use, and there have been post-marketing reports of chondrolysis in patients receiving such infusions. The majority of reported cases of chondrolysis have involved the shoulder joint; cases of gleno-humeral chondrolysis have been described in pediatric and adult patients following intra-articular infusions of local anesthetics with and without epinephrine for periods of 48 to 72 hours. There is insufficient information to determine whether shorter infusion periods are not associated with these findings. The time of onset of symptoms, such as joint pain, stiffness and loss of motion can be variable, but may begin as early as the 2nd month after surgery. Currently, there is no effective treatment for chondrolysis; patients who experienced chondrolysis have required additional diagnostic and therapeutic procedures and some required arthroplasty or shoulder replacement.

To avoid intravascular injection, aspiration should be performed before the local anesthetic solution is injected. The needle must be repositioned until no return of blood can be elicited by aspiration. Note, however, that the absence of blood in the syringe does not guarantee that intravascular injection has been avoided.

Local anesthetic solutions containing antimicrobial preservatives (e.g., methylparaben) should not be used for epidural or spinal anesthesia because the safety of these agents has not been established with regard to intrathecal injection, either intentional or accidental.

PRECAUTIONS

<paragraph>PRECAUTIONSGeneral:

The safety and effectiveness of lidocaine depend on proper dosage, correct technique, adequate precautions, and readiness for emergencies. Standard textbooks should be consulted for specific techniques and precautions for various regional anesthetic procedures.

Resuscitative equipment, oxygen, and other resuscitative drugs should be available for immediate use. (See WARNINGS and ADVERSE REACTIONS). The lowest dosage that results in effective anesthesia should be used to avoid high plasma levels and serious adverse effects. Syringe aspirations should also be performed before and during each supplemental injection when using indwelling catheter techniques. During the administration of epidural anesthesia, it is recommended that a test dose be administered initially and that the patient be monitored for central nervous system toxicity and cardiovascular toxicity, as well as for signs of unintended intrathecal administration before proceeding. When clinical conditions permit, consideration should be given to employing local anesthetic solutions that contain epinephrine for the test dose because circulatory changes compatible with epinephrine may also serve as a warning sign of unintended intravascular injection. An intravascular injection is still possible even if aspirations for blood are negative. Repeated doses of lidocaine may cause significant increases in blood levels with each repeated dose because of slow accumulation of the drug or its metabolites. Tolerance to elevated blood levels varies with the status of the patient. Debilitated, elderly patients, acutely ill patients and children should be given reduced doses commensurate with their age and physical condition. Lidocaine should also be used with caution in patients with severe shock or heart block. Lumbar and caudal epidural anesthesia should be used with extreme caution in persons with the following conditions: existing neurological disease, spinal deformities, septicemia and severe hypertension.

Local anesthetic solutions containing a vasoconstrictor should be used cautiously and in carefully circumscribed quantities in areas of the body supplied by end arteries or having otherwise compromised blood supply. Patients with peripheral vascular disease and those with hypertensive vascular disease may exhibit exaggerated vasoconstrictor response. Ischemic injury or necrosis may result. Preparations containing a vasoconstrictor should be used with caution in patients during or following the administration of potent general anesthetic agents, since cardiac arrhythmias may occur under such conditions.

Careful and constant monitoring of cardiovascular and respiratory (adequacy of ventilation) vital signs and the patient’s state of consciousness should be accomplished after each local anesthetic injection. It should be kept in mind at such times that restlessness, anxiety, tinnitus, dizziness, blurred vision, tremors, depression or drowsiness may be early warning signs of central nervous system toxicity.

Since amide-type local anesthetics are metabolized by the liver, lidocaine should be used with caution in patients with hepatic disease. Patients with severe hepatic disease, because of their inability to metabolize local anesthetics normally, are at greater risk of developing toxic plasma concentrations. Lidocaine should also be used with caution in patients with impaired cardiovascular function since they may be less able to compensate for functional changes associated with the prolongation of A-V conduction produced by these drugs. Many drugs used during the conduct of anesthesia are considered potential triggering agents for familial malignant hyperthermia. Since it is not known whether amide-type local anesthetics may trigger this reaction and since the need for supplemental general anesthesia cannot be predicted in advance, it is suggested that a standard protocol for the management of malignant hyperthermia should be available. Early unexplained signs of tachycardia, tachypnea, labile blood pressure and metabolic acidosis may precede temperature elevation. Successful outcome is dependent on early diagnosis, prompt discontinuance of the suspect triggering agent(s) and institution of treatment, including oxygen therapy, indicated supportive measures and dantrolene (consult dantrolene sodium intravenous package insert before using).

Proper tourniquet technique, as described in publications and standard textbooks, is essential in the performance of intravenous regional anesthesia. Solutions containing epinephrine or other vasoconstrictors should not be used for this technique.

Lidocaine should be used with caution in persons with known drug sensitivities. Patients allergic to para-aminobenzoic acid derivatives (procaine, tetracaine, benzocaine, etc.) have not shown cross sensitivity to lidocaine.

Use in the Head and Neck Area: Small doses of local anesthetics injected into the head and neck area, including retrobulbar, dental and stellate ganglion blocks, may produce adverse reactions similar to systemic toxicity seen with unintentional intravascular injections of larger doses. Confusion, convulsions, respiratory depression and/or respiratory arrest and cardiovascular stimulation or depression have been reported. These reactions may be due to intra-arterial injections of the local anesthetic with retrograde flow to the cerebral circulation. Patients receiving these blocks should have their circulation and respiration monitored and be constantly observed. Resuscitative equipment and personnel for treating adverse reactions should be immediately available. Dosage recommendations should not be exceeded. (See DOSAGE AND ADMINISTRATION).

Information for Patients:

When appropriate, patients should be informed in advance that they may experience temporary loss of sensation and motor activity, usually in the lower half of the body following proper administration of epidural anesthesia.

Clinically Significant Drug Interactions:

The administration of local anesthetic solutions containing epinephrine or norepinephrine to patients receiving monoamine oxidase inhibitors or tricyclic antidepressants may produce severe prolonged hypertension.

Phenothiazines and butyrophenones may reduce or reverse the pressor effect of epinephrine.

Concurrent use of these agents should generally be avoided. In situations when concurrent therapy is necessary, careful patient monitoring is essential.

Concurrent administration of vasopressor drugs (for the treatment of hypotension related to obstetric blocks) and ergot-type oxytoxic drugs may cause severe persistent hypertension or cerebrovascular accidents.

Drug Laboratory Test Interactions:

The intramuscular injection of lidocaine may result in an increase in creatine phosphokinase levels. Thus, the use of this enzyme determination without isoenzyme separation as a diagnostic test for the presence of acute myocardial infarction may be compromised by the intramuscular injection of lidocaine.

Carcinogenesis, Mutagenesis, Impairment of Fertility:

Studies of lidocaine in animals to evaluate the carcinogenic and mutagenic potential or the effect on fertility have not been conducted.

Pregnancy:

Teratogenic Effects. Pregnancy Category B. Reproduction studies have been performed in rats at doses up to 6.6 times the human dose and have revealed no evidence of harm to the fetus caused by lidocaine. There are, however, no adequate and well-controlled studies in pregnant women. Animal reproduction studies are not always predictive of human response. General consideration should be given to this fact before administering lidocaine to women of childbearing potential, especially during early pregnancy when maximum organogenesis takes place.

Labor and Delivery:

Local anesthetics rapidly cross the placenta and when used for epidural, paracervical, pudendal or caudal block anesthesia, can cause varying degrees of maternal, fetal and neonatal toxicity (See CLINICAL PHARMACOLOGY—Pharmacokinetics). The potential for toxicity depends upon the procedure performed, the type and amount of drug used, and the technique of drug administration. Adverse reactions in the parturient, fetus and neonate involve alterations of the central nervous system peripheral vascular tone and cardiac function.

Maternal hypotension has resulted from regional anesthesia. Local anesthetics produce vasodilation by blocking sympathetic nerves. Elevating the patient’s legs and positioning her on her left side will help prevent decreases in blood pressure. The fetal heart rate also should be monitored continuously, and electronic fetal monitoring is highly advisable.

Epidural, spinal, paracervical, or pudendal anesthesia may alter the forces of parturition through changes in uterine contractility or maternal expulsive efforts. In one study, paracervical block anesthesia was associated with a decrease in the mean duration of first stage labor and facilitation of cervical dilation. However, spinal and epidural anesthesia have also been reported to prolong the second stage of labor by removing the parturient’s reflex urge to bear down or by interfering with motor function. The use of obstetrical anesthesia may increase the need for forceps assistance.

The use of some local anesthetic drug products during labor and delivery may be followed by diminished muscle strength and tone for the first day or two of life. The long-term significance of these observations is unknown. Fetal bradycardia may occur in 20 to 30 percent of patients receiving paracervical nerve block anesthesia with the amide-type local anesthetics and may be associated with fetal acidosis. Fetal heart rate should always be monitored during paracervical anesthesia. The physician should weigh the possible advantages against risks when considering paracervical block in prematurity, toxemia of pregnancy and fetal distress. Careful adherence to recommended dosage is of the utmost importance in obstetrical paracervical block. Failure to achieve adequate analgesia with recommended doses should arouse suspicion of intravascular or fetal intracranial injection. Cases compatible with unintended fetal intracranial injection of local anesthetic solution have been reported following intended paracervical or pudendal block or both. Babies so affected present with unexplained neonatal depression at birth, which correlates with high local anesthetic serum levels, and often manifest seizures within six hours. Prompt use of supportive measures combined with forced urinary excretion of the local anesthetic has been used successfully to manage this complication.

Case reports of maternal convulsions and cardiovascular collapse following use of some local anesthetics for paracervical block in early pregnancy (as anesthesia for elective abortion) suggest that systemic absorption under these circumstances may be rapid. The recommended maximum dose of each drug should not be exceeded. Injection should be made slowly and with frequent aspiration. Allow a 5-minute interval between sides.

Nursing Mothers:

It is not known whether this drug is excreted in human milk. Because many drugs are excreted in human milk, caution should be exercised when lidocaine is administered to a nursing woman.

Pediatric Use:

Dosages in pediatric patients should be reduced, commensurate with age, body weight and physical condition. See DOSAGE AND ADMINISTRATION.

ADVERSE REACTIONS

Systemic: Adverse experiences following the administration of lidocaine are similar in nature to those observed with other amide local anesthetic agents. These adverse experiences are, in general, dose-related and may result from high plasma levels caused by excessive dosage, rapid absorption or inadvertent intravascular injection, or may result from a hypersensitivity, idiosyncrasy or diminished tolerance on the part of the patient. Serious adverse experiences are generally systemic in nature. The following types are those most commonly reported:

Central Nervous System: CNS manifestations are excitatory and/or depressant and may be characterized by lightheadedness, nervousness, apprehension, euphoria, confusion, dizziness, drowsiness, tinnitus, blurred or double vision, vomiting, sensations of heat, cold or numbness, twitching, tremors, convulsions, unconsciousness, respiratory depression and arrest. The excitatory manifestations may be very brief or may not occur at all, in which case the first manifestation of toxicity may be drowsiness merging into unconsciousness and respiratory arrest.

Drowsiness following the administration of lidocaine is usually an early sign of a high blood level of the drug and may occur as a consequence of rapid absorption.

Cardiovascular System: Cardiovascular manifestations are usually depressant and are characterized by bradycardia, hypotension, and cardiovascular collapse, which may lead to cardiac arrest.

Allergic: Allergic reactions are characterized by cutaneous lesions, urticaria, edema or anaphylactoid reactions. Allergic reactions may occur as a result of sensitivity either to local anesthetic agents or to the methylparaben used as a preservative in multiple dose vials. Allergic reactions as a result of sensitivity to lidocaine are extremely rare and, if they occur, should be managed by conventional means. The detection of sensitivity by skin testing is of doubtful value.

Neurologic: The incidences of adverse reactions associated with the use of local anesthetics may be related to the total dose of local anesthetic administered and are also dependent upon the particular drug used, the route of administration and the physical status of the patient. In a prospective review of 10,440 patients who received lidocaine for spinal anesthesia, the incidences of adverse reactions were reported to be about 3 percent each for positional headaches, hypotension and backache; 2 percent for shivering; and less than 1 percent each for peripheral nerve symptoms, nausea, respiratory inadequacy and double vision. Many of these observations may be related to local anesthetic techniques, with or without a contribution from the local anesthetic.

In the practice of caudal or lumbar epidural block, occasional unintentional penetration of the subarachnoid space by the catheter may occur. Subsequent adverse effects may depend partially on the amount of drug administered subdurally.

These may include spinal block of varying magnitude (including total spinal block), hypotension secondary to spinal block, loss of bladder and bowel control, and loss of perineal sensation and sexual function. Persistent motor, sensory and/or autonomic (sphincter control) deficit of some lower spinal segments with slow recovery (several months) or incomplete recovery have been reported in rare instances when caudal or lumbar epidural block has been attempted. Backache and headache have also been noted following use of these anesthetic procedures.

There have been reported cases of permanent injury to extraocular muscles requiring surgical repair following retrobulbar administration.

OVERDOSAGE

Acute emergencies from local anesthetics are generally related to high plasma levels encountered during therapeutic use of local anesthetics or to unintended subarachnoid injection of local anesthetic solution (see ADVERSE REACTIONS, WARNINGS and PRECAUTIONS).

Management of Local Anesthetic Emergencies: The first consideration is prevention, best accomplished by careful monitoring of cardiovascular and respiratory vital signs and the patient’s state of consciousness after each local anesthetic injection. At the first sign of change, oxygen should be administered.

The first step in the management of convulsions, as well as underventilation or apnea due to unintended subarachnoid injection of drug solution, consists of immediate attention to the maintenance of a patent airway and assisted or controlled ventilation with oxygen and a delivery system capable of permitting immediate positive airway pressure by mask. Immediately after the institution of these ventilatory measures, the adequacy of the circulation should be evaluated, keeping in mind that drugs used to treat convulsions sometimes depress the circulation when administered intravenously. Should convulsions persist despite adequate respiratory support, and if the status of the circulation permits, small increments of an ultra-short acting barbiturate (such as thiopental or thiamylal) or a benzodiazepine (such as diazepam) may be administered intravenously. The clinician should be familiar, prior to use of local anesthetics, with these anticonvulsant drugs. Supportive treatment of circulatory depression may require administration of intravenous fluids and, when appropriate, a vasopressor as directed by the clinical situation (e.g., ephedrine).

If not treated immediately, both convulsions and cardiovascular depression can result in hypoxia, acidosis, bradycardia, arrhythmias and cardiac arrest. Underventilation or apnea due to unintentional subarachnoid injection of local anesthetic solution may produce these same signs and also lead to cardiac arrest if ventilatory support is not instituted. If cardiac arrest should occur standard cardiopulmonary resuscitative measures should be instituted.

Endotracheal intubation, employing drugs and techniques familiar to the clinician, may be indicated, after initial administration of oxygen by mask, if difficulty is encountered in the maintenance of a patent airway or if prolonged ventilatory support (assisted or controlled) is indicated.

Dialysis is of negligible value in the treatment of acute overdosage with lidocaine.

The oral LD50 of lidocaine HCl in non-fasted female rats is 459 (346−773) mg/kg (as the salt) and 214 (159−324) mg/kg (as the salt) in fasted female rats.

DOSAGE AND ADMINISTRATION

Table 1 (Recommended Dosages) summarizes the recommended volumes and concentrations of Lidocaine Hydrochloride Injection, USP for various types of anesthetic procedures. The dosages suggested in this table are for normal healthy adults and refer to the use of epinephrine-free solutions. When larger volumes are required only solutions containing epinephrine should be used, except in those cases where vasopressor drugs may be contraindicated.

There have been adverse event reports of chondrolysis in patients receiving intra-articular infusions of local anesthetics following arthroscopic and other surgical procedures. Lidocaine is not approved for this use (see WARNINGS and DOSAGE AND ADMINISTRATION).

These recommended doses serve only as a guide to the amount of anesthetic required for most routine procedures. The actual volumes and concentrations to be used depend on a number of factors such as type and extent of surgical procedure, depth of anesthesia and degree of muscular relaxation required, duration of anesthesia required, and the physical condition of the patient. In all cases the lowest concentration and smallest dose that will produce the desired result should be given. Dosages should be reduced for children and for elderly and debilitated patients and patients with cardiac and/or liver disease.

The onset of anesthesia, the duration of anesthesia and the degree of muscular relaxation are proportional to the volume and concentration (i.e., total dose) of local anesthetic used. Thus, an increase in volume and concentration of Lidocaine Hydrochloride Injection will decrease the onset of anesthesia, prolong the duration of anesthesia, provide a greater degree of muscular relaxation and increase the segmental spread of anesthesia. However, increasing the volume and concentration of Lidocaine Hydrochloride Injection may result in a more profound fall in blood pressure when used in epidural anesthesia. Although the incidence of side effects with lidocaine is quite low, caution should be exercised when employing large volumes and concentrations, since the incidence of side effects is directly proportional to the total dose of local anesthetic agent injected.

For intravenous regional anesthesia, only the 50 mL single-dose vial containing 0.5% Lidocaine Hydrochloride Injection, USP should be used.

Epidural Anesthesia

For epidural anesthesia, only the following available specific products of Lidocaine Hydrochloride Injection by Hospira are recommended:

1%. . . . . . . . . . . . . . . . . . . . 30 mL single-dose teartop vials

1.5%. . . . . . . . . . . . . . . . . . . . . . . 20 mL single-dose ampuls

2%. . . . . . . . . . . . . . . . . . . . . . . . . 10 mL single-dose ampuls

Although these solutions are intended specifically for epidural anesthesia, they may also be used for infiltration and peripheral nerve block provided they are employed as single dose units. These solutions contain no bacteriostatic agent. In epidural anesthesia, the dosage varies with the number of dermatomes to be anesthetized (generally 2−3 mL of the indicated concentration per dermatome).

Caudal and Lumbar Epidural Block: As a precaution against the adverse experiences sometimes observed following unintentional penetration of the subarachnoid space, a test dose such as 2−3 mL of 1.5% lidocaine hydrochloride should be administered at least 5 minutes prior to injecting the total volume required for a lumbar or caudal epidural block. The test dose should be repeated if the patient is moved in a manner that may have displaced the catheter. Epinephrine, if contained in the test dose (10−15 mcg have been suggested), may serve as a warning of unintentional intravascular injection. If injected into a blood vessel, this amount of epinephrine is likely to produce a transient "epinephrine response" within 45 seconds, consisting of an increase in heart rate and systolic blood pressure, circumoral pallor, palpitations and nervousness in the unsedated patient. The sedated patient may exhibit only a pulse rate increase of 20 or more beats per minute for 15 or more seconds. Patients on beta-blockers may not manifest changes in heart rate, but blood pressure monitoring can detect an evanescent rise in systolic blood pressure. Adequate time should be allowed for onset of anesthesia after administration of each test dose. The rapid injection of a large volume of Lidocaine Hydrochloride Injection through the catheter should be avoided, and, when feasible, fractional doses should be administered.

In the event of the known injection of a large volume of local anesthetic solutions into the subarachnoid space, after suitable resuscitation and if the catheter is in place, consider attempting the recovery of drug by draining a moderate amount of cerebrospinal fluid (such as 10 mL) through the epidural catheter.

Maximum Recommended Dosages

NOTE: The products accompanying this insert do not contain epinephrine.

Adults: For normal healthy adults, the individual maximum recommended dose of lidocaine HCl with epinephrine should not exceed 7 mg/kg (3.5 mg/lb) of body weight and in general it is recommended that the maximum total dose not exceed 500 mg. When used without epinephrine, the maximum individual dose should not exceed 4.5 mg/kg (2 mg/lb) of body weight and in general it is recommended that the maximum total dose does not exceed 300 mg. For continuous epidural or caudal anesthesia, the maximum recommended dosage should not be administered at intervals of less than 90 minutes. When continuous lumbar or caudal epidural anesthesia is used for non-obstetrical procedures, more drug may be administered if required to produce adequate anesthesia.

The maximum recommended dose per 90 minute period of lidocaine hydrochloride for paracervical block in obstetrical patients and non-obstetrical patients is 200 mg total. One-half of the total dose is usually administered to each side. Inject slowly five minutes between sides. (See also discussion of paracervical block in PRECAUTIONS).

For intravenous regional anesthesia, the dose administered should not exceed 4 mg/kg in adults.

Children: It is difficult to recommend a maximum dose of any drug for children, since this varies as a function of age and weight. For children over 3 years of age who have a normal lean body mass and normal body development, the maximum dose is determined by the child’s age and weight. For example, in a child of 5 years weighing 50 lbs., the dose of lidocaine HCl should not exceed 75 — 100 mg (1.5 — 2 mg/lb). The use of even more dilute solutions (i.e., 0.25 — 0.5%) and total dosages not to exceed 3 mg/kg (1.4 mg/lb) are recommended for induction of intravenous regional anesthesia in children.

In order to guard against systemic toxicity, the lowest effective concentration and lowest effective dose should be used at all times. In some cases it will be necessary to dilute available concentrations with 0.9% sodium chloride injection in order to obtain the required final concentration.

Parenteral drug products should be inspected visually for particulate matter and discoloration prior to administration whenever the solution and container permit. Solutions that are discolored and/or contain particulate matter should not be used.

Table 1
Recommended Dosages of Lidocaine Hydrochloride Injection, USP for Various Anesthetic
Procedures in Normal Healthy Adults
 | Lidocaine Hydrochloride Injection, USP (without Epinephrine)
Procedure | Conc. (%) | Vol. (mL) | Total Dose (mg)
Infiltration
Percutaneous | 0.5 or 1.0 | 1−60 | 5−300
Intravenous Regional | 0.5 | 10−60 | 50−300
Peripheral Nerve Blocks, e.g.
Brachial | 1.5 | 15−20 | 225−300
Dental | 2.0 | 1−5 | 20−100
Intercostal | 1.0 | 3 | 30
Paravertebral | 1.0 | 3−5 | 30−50
Pudendal (each side) | 1.0 | 10 | 100
Paracervical
Obstetrical Analgesia
(each side) | 1.0 | 10 | 100
Sympathetic Nerve Blocks, e.g.
Cervical (stellate ganglion) | 1.0 | 5 | 50
Lumbar | 1.0 | 5−10 | 50−100
Central Neural Blocks
Epidural*
Thoracic | 1.0 | 20−30 | 200−300
Lumbar
Analgesia | 1.0 | 25−30 | 250−300
Anesthesia | 1.5 | 15−20 | 225−300
 | 2.0 | 10−15 | 200−300
Caudal
Obstetrical Analgesia | 1.0 | 20−30 | 200−300
Surgical Anesthesia | 1.5 | 15−20 | 225−300
*Dose determined by number of dermatomes to be anesthetized (2 to 3 mL/dermatome).

THE ABOVE SUGGESTED CONCENTRATIONS AND VOLUMES SERVE ONLY AS A GUIDE. OTHER VOLUMES AND CONCENTRATIONS MAY BE USED PROVIDED THE TOTAL MAXIMUM RECOMMENDED DOSE IS NOT EXCEEDED.

Sterilization, Storage and Technical Procedures: Disinfecting agents containing heavy metals, which cause release of respective ions (mercury, zinc, copper, etc.) should not be used for skin or mucous membrane disinfection as they have been related to incidence of swelling and edema. When chemical disinfection of multi-dose vials is desired, either isopropyl alcohol (91%) or 70% ethyl alcohol is recommended. Many commercially available brands of rubbing alcohol, as well as solutions of ethyl alcohol not of USP grade, contain denaturants which are injurious to rubber and, therefore, are not to be used. It is recommended that chemical disinfection be accomplished by wiping the vial stopper thoroughly with cotton or gauze that has been moistened with the recommended alcohol just prior to use.

HOW SUPPLIED

Lidocaine Hydrochloride Injection, USP is supplied as follows:

NDC | Container | Concentration | Size | Total (mg)
Single-dose:
0409-4278-01 | Glass Teartop Vial | 0.5% (5 mg/mL) | 50 mL | 250
0409-4713-01 | Glass Ampul | 1% (10 mg/mL) | 2 mL (bulk – 400 units) | 20
0409-4713-02 | Glass Ampul | 1% (10 mg/mL) | 5 mL | 50
0409-4713-05 | Glass Ampul | 1% (10 mg/mL) | 5 mL (bulk – 400 units) | 50
0409-4713-20 | Glass Ampul | 1% (10 mg/mL) | 20 mL | 200
0409-4713-32 | Glass Ampul | 1% (10 mg/mL) | 2 mL | 20
0409-4713-62 | Glass Ampul | 1% (10 mg/mL) | 2 mL (bulk – 800 units) | 20
0409-4713-65 | Glass Ampul | 1% (10 mg/mL) | 5 mL (bulk – 800 units) | 50
0409-4279-02 | Glass Teartop Vial | 1% (10 mg/mL) | 30 mL | 300
0409-4270-01 | Sterile Glass Teartop Vial | 1% (10 mg/mL) | 30 mL | 300
0409-4776-01 | Glass Ampul | 1.5% (15 mg/mL) | 20 mL | 300
0409-4056-01 | Sterile Glass Ampul | 1.5% (15 mg/mL) | 20 mL | 300
0409-4282-01 | Glass Ampul | 2% (20 mg/mL) | 2 mL | 40
0409-4282-02 | Glass Ampul | 2% (20 mg/mL) | 10 mL | 200
Multiple-dose:
0409-4275-01 | Plastic Fliptop Vial | 0.5% (5 mg/mL) | 50 mL | 250
0409-4276-01 | Plastic Fliptop Vial | 1% (10 mg/mL) | 20 mL | 200
0409-4276-02 | Plastic Fliptop Vial | 1% (10 mg/mL) | 50 mL | 500
0409-4277-01 | Plastic Fliptop Vial | 2% (20 mg/mL) | 20 mL | 400
0409-4277-02 | Plastic Fliptop Vial | 2% (20 mg/mL) | 50 mL | 1000

Single-dose products are preservative-free.

Store at 20 to 25°C (68 to 77°F). [See USP Controlled Room Temperature.]

Lidocaine Hydrochloride Injection, USP solutions packaged in ampuls and glass teartop vials may be autoclaved one time only. Autoclave at 15 pounds pressure, 121°C (250°F) for 15 minutes. DO NOT AUTOCLAVE PRODUCT IN PLASTIC VIALS.

Revised: February, 2010

Printed in USA EN-2421

Hospira, Inc., Lake Forest, IL 60045 USA

DESCRIPTION

<paragraph>

MARCAINE SPINAL (bupivacaine hydrochloride) injection, solution
[Hospira, Inc.]

bupivacaine hydrochloride in dextrose injection, USP

STERILE HYPERBARIC SOLUTION

FOR SPINAL ANESTHESIA

Rx only

DESCRIPTION

Bupivacaine hydrochloride is 2-Piperidinecarboxamide, 1-butyl-N-(2,6-dimethylphenyl)-, monohydrochloride, monohydrate, a white crystalline powder that is freely soluble in 95 percent ethanol, soluble in water, and slightly soluble in chloroform or acetone. It has the following structural formula:

Dextrose is D-glucopyranose monohydrate and has the following structural formula:

MARCAINETM Spinal is available in sterile hyperbaric solution for subarachnoid injection (spinal block).

Bupivacaine hydrochloride is related chemically and pharmacologically to the aminoacyl local anesthetics. It is a homologue of mepivacaine and is chemically related to lidocaine. All three of these anesthetics contain an amide linkage between the aromatic nucleus and the amino or piperidine group. They differ in this respect from the procaine-type local anesthetics, which have an ester linkage.

Each mL of MARCAINE Spinal contains 7.5 mg bupivacaine hydrochloride (anhydrous) and 82.5 mg dextrose (anhydrous). The pH of this solution is adjusted to between 4.0 and 6.5 with sodium hydroxide or hydrochloric acid.

The specific gravity of MARCAINE Spinal is between 1.030 and 1.035 at 25°C and 1.03 at 37°C.

MARCAINE Spinal does not contain any preservatives.

<paragraph>CLINICAL PHARMACOLOGY

Local anesthetics block the generation and the conduction of nerve impulses, presumably by increasing the threshold for electrical excitation in the nerve, by slowing the propagation of the nerve impulse, and by reducing the rate of rise of the action potential. In general, the progression of anesthesia is related to the diameter, myelination, and conduction velocity of affected nerve fibers. Clinically, the order of loss of nerve function is as follows: (1) pain, (2) temperature, (3) touch, (4) proprioception, and (5) skeletal muscle tone.

Systemic absorption of local anesthetics produces effects on the cardiovascular and central nervous systems (CNS). At blood concentrations achieved with normal therapeutic doses, changes in cardiac conduction, excitability, refractoriness, contractility, and peripheral vascular resistance are minimal. However, toxic blood concentrations depress cardiac conduction and excitability, which may lead to atrioventricular block, ventricular arrhythmias, and cardiac arrest, sometimes resulting in fatalities. In addition, myocardial contractility is depressed and peripheral vasodilation occurs, leading to decreased cardiac output and arterial blood pressure. Recent clinical reports and animal research suggest that these cardiovascular changes are more likely to occur after unintended direct intravascular injection of bupivacaine. Therefore, when epidural anesthesia with bupivacaine is considered, incremental dosing is necessary.

Following systemic absorption, local anesthetics can produce central nervous system stimulation, depression, or both. Apparent central stimulation is manifested as restlessness, tremors and shivering, progressing to convulsions, followed by depression and coma progressing ultimately to respiratory arrest. However, the local anesthetics have a primary depressant effect on the medulla and on higher centers. The depressed stage may occur without a prior excited stage.

Pharmacokinetics: The rate of systemic absorption of local anesthetics is dependent upon the total dose and concentration of drug administered, the route of administration, the vascularity of the administration site, and the presence or absence of epinephrine in the anesthetic solution. A dilute concentration of epinephrine (1:200,000 or 5 mcg/mL) usually reduces the rate of absorption and peak plasma concentration of MARCAINE, permitting the use of moderately larger total doses and sometimes prolonging the duration of action.

The onset of action with MARCAINE is rapid and anesthesia is long lasting. The duration of anesthesia is significantly longer with MARCAINE than with any other commonly used local anesthetic. It has also been noted that there is a period of analgesia that persists after the return of sensation, during which time the need for strong analgesics is reduced.

The onset of sensory blockade following spinal block with MARCAINE Spinal is very rapid (within one minute); maximum motor blockade and maximum dermatome level are achieved within 15 minutes in most cases. Duration of sensory blockade (time to return of complete sensation in the operative site or regression of two dermatomes) following a 12 mg dose averages 2 hours with or without 0.2 mg epinephrine. The time to return of complete motor ability with 12 mg MARCAINE Spinal averages 3 1/2 hours without the addition of epinephrine and 4 1/2 hours if 0.2 mg epinephrine is added. When compared to equal milligram doses of hyperbaric tetracaine, the duration of sensory blockade was the same but the time to complete motor recovery was significantly longer for tetracaine. Addition of 0.2 mg epinephrine significantly prolongs the motor blockade and time to first postoperative narcotic with MARCAINE Spinal.

Local anesthetics appear to cross the placenta by passive diffusion. The rate and degree of diffusion is governed by (1) the degree of plasma protein binding, (2) the degree of ionization, and (3) the degree of lipid solubility. Fetal/maternal ratios of local anesthetics appear to be inversely related to the degree of plasma protein binding, because only the free, unbound drug is available for placental transfer. MARCAINE with a high protein binding capacity (95%) has a low fetal/maternal ratio (0.2 to 0.4). The extent of placental transfer is also determined by the degree of ionization and lipid solubility of the drug. Lipid soluble, nonionized drugs readily enter the fetal blood from the maternal circulation.

Depending upon the route of administration, local anesthetics are distributed to some extent to all body tissues, with high concentrations found in highly perfused organs such as the liver, lungs, heart, and brain.

Pharmacokinetic studies on the plasma profiles of MARCAINE after direct intravenous injection suggest a three-compartment open model. The first compartment is represented by the rapid intravascular distribution of the drug. The second compartment represents the equilibration of the drug throughout the highly perfused organs such as the brain, myocardium, lungs, kidneys, and liver. The third compartment represents an equilibration of the drug with poorly perfused tissues, such as muscle and fat. The elimination of drug from tissue distribution depends largely upon the ability of binding sites in the circulation to carry it to the liver where it is metabolized.

Various pharmacokinetic parameters of the local anesthetics can be significantly altered by the presence of hepatic or renal disease, addition of epinephrine, factors affecting urinary pH, renal blood flow, the route of drug administration, and the age of the patient. The half-life of MARCAINE in adults is 2.7 hours and in neonates 8.1 hours. In clinical studies, elderly patients exhibited a greater spread and higher maximal level of analgesia than younger patients. Elderly patients also reached the maximal level of analgesia more rapidly than younger patients, and exhibited a faster onset of motor blockade. The total plasma clearance was decreased and the terminal half-life was lengthened in these patients.

Amide-type local anesthetics such as MARCAINE are metabolized primarily in the liver via conjugation with glucuronic acid. Patients with hepatic disease, especially those with severe hepatic disease, may be more susceptible to the potential toxicities of the amide-type local anesthetics. Pipecolylxylidine is the major metabolite of MARCAINE.

The kidney is the main excretory organ for most local anesthetics and their metabolites. Urinary excretion is affected by urinary perfusion and factors affecting urinary pH. Only 6% of bupivacaine is excreted unchanged in the urine.

When administered in recommended doses and concentrations, MARCAINE does not ordinarily produce irritation or tissue damage and does not cause methemoglobinemia.

<paragraph>INDICATIONS AND USAGE

MARCAINE Spinal is indicated for the production of subarachnoid block (spinal anesthesia).

Standard textbooks should be consulted to determine the accepted procedures and techniques for the administration of spinal anesthesia.

<paragraph>CONTRAINDICATIONS

MARCAINE Spinal is contraindicated in patients with a known hypersensitivity to it or to any local anesthetic agent of the amide-type.

The following conditions preclude the use of spinal anesthesia:

1. Severe hemorrhage, severe hypotension or shock and arrhythmias, such as complete heart block, which severely restrict cardiac output.
2. Local infection at the site of proposed lumbar puncture.
3. Septicemia.

<paragraph>WARNINGS

LOCAL ANESTHETICS SHOULD ONLY BE EMPLOYED BY CLINICIANS WHO ARE WELL VERSED IN DIAGNOSIS AND MANAGEMENT OF DOSE-RELATED TOXICITY AND OTHER ACUTE EMERGENCIES WHICH MIGHT ARISE FROM THE BLOCK TO BE EMPLOYED, AND THEN ONLY AFTER INSURING THE IMMEDIATE AVAILABILITY OF OXYGEN, OTHER RESUSCITATIVE DRUGS, CARDIOPULMONARY RESUSCITATIVE EQUIPMENT, AND THE PERSONNEL RESOURCES NEEDED FOR PROPER MANAGEMENT OF TOXIC REACTIONS AND RELATED EMERGENCIES. (See also ADVERSE REACTIONS and PRECAUTIONS.) DELAY IN PROPER MANAGEMENT OF DOSE-RELATED TOXICITY, UNDERVENTILATION FROM ANY CAUSE AND/OR ALTERED SENSITIVITY MAY LEAD TO THE DEVELOPMENT OF ACIDOSIS, CARDIAC ARREST, AND, POSSIBLY, DEATH.

Intra-articular infusions of local anesthetics following arthroscopic and other surgical procedures is an unapproved use, and there have been post-marketing reports of chondrolysis in patients receiving such infusions. The majority of reported cases of chondrolysis have involved the shoulder joint; cases of gleno-humeral chondrolysis have been described in pediatric and adult patients following intra-articular infusions of local anesthetics with and without epinephrine for periods of 48 to 72 hours. There is insufficient information to determine whether shorter infusion periods are not associated with these findings. The time of onset of symptoms, such as joint pain, stiffness and loss of motion can be variable, but may begin as early as the 2nd month after surgery. Currently, there is no effective treatment for chondrolysis; patients who experienced chondrolysis have required additional diagnostic and therapeutic procedures and some required arthroplasty or shoulder replacement.

Spinal anesthetics should not be injected during uterine contractions, because spinal fluid current may carry the drug further cephalad than desired.

A free flow of cerebrospinal fluid during the performance of spinal anesthesia is indicative of entry into the subarachnoid space. However, aspiration should be performed before the anesthetic solution is injected to confirm entry into the subarachnoid space and to avoid intravascular injection.

MARCAINE solutions containing epinephrine or other vasopressors should not be used concomitantly with ergot-type oxytocic drugs, because a severe persistent hypertension may occur. Likewise, solutions of MARCAINE containing a vasoconstrictor, such as epinephrine, should be used with extreme caution in patients receiving monoamine oxidase inhibitors (MAOI) or antidepressants of the triptyline or imipramine types, because severe prolonged hypertension may result.

Until further experience is gained in patients younger than 18 years, administration of MARCAINE in this age group is not recommended.

Mixing or the prior or intercurrent use of any other local anesthetic with MARCAINE cannot be recommended because of insufficient data on the clinical use of such mixtures.

<paragraph>PRECAUTIONS

General: The safety and effectiveness of spinal anesthetics depend on proper dosage, correct technique, adequate precautions, and readiness for emergencies. Resuscitative equipment, oxygen, and other resuscitative drugs should be available for immediate use. (See WARNINGS and ADVERSE REACTIONS.) The patient should have IV fluids running via an indwelling catheter to assure a functioning intravenous pathway. The lowest dosage of local anesthetic that results in effective anesthesia should be used. Aspiration for blood should be performed before injection and injection should be made slowly. Tolerance varies with the status of the patient. Elderly patients and acutely ill patients may require reduced doses. Reduced doses may also be indicated in patients with increased intra-abdominal pressure (including obstetrical patients), if otherwise suitable for spinal anesthesia.

There should be careful and constant monitoring of cardiovascular and respiratory (adequacy of ventilation) vital signs and the patient’s state of consciousness after local anesthetic injection. Restlessness, anxiety, incoherent speech, lightheadedness, numbness and tingling of the mouth and lips, metallic taste, tinnitus, dizziness, blurred vision, tremors, depression, or drowsiness may be early warning signs of central nervous system toxicity.

Spinal anesthetics should be used with caution in patients with severe disturbances of cardiac rhythm, shock, or heart block.

Sympathetic blockade occurring during spinal anesthesia may result in peripheral vasodilation and hypotension, the extent depending on the number of dermatomes blocked. Patients over 65 years, particularly those with hypertension, may be at increased risk for experiencing the hypotensive effects of MARCAINE Spinal. Blood pressure should, therefore, be carefully monitored especially in the early phases of anesthesia. Hypotension may be controlled by vasoconstrictors in dosages depending on the severity of hypotension and response of treatment. The level of anesthesia should be carefully monitored because it is not always controllable in spinal techniques.

Because amide-type local anesthetics such as MARCAINE are metabolized by the liver, these drugs, especially repeat doses, should be used cautiously in patients with hepatic disease. Patients with severe hepatic disease, because of their inability to metabolize local anesthetics normally, are at a greater risk of developing toxic plasma concentrations. Local anesthetics should also be used with caution in patients with impaired cardiovascular function because they may be less able to compensate for functional changes associated with the prolongation of AV conduction produced by these drugs. However, dosage recommendations for spinal anesthesia are much lower than dosage recommendations for other major blocks and most experience regarding hepatic and cardiovascular disease dose-related toxicity is derived from these other major blocks.

Serious dose-related cardiac arrhythmias may occur if preparations containing a vasoconstrictor such as epinephrine are employed in patients during or following the administration of potent inhalation agents. In deciding whether to use these products concurrently in the same patient, the combined action of both agents upon the myocardium, the concentration and volume of vasoconstrictor used, and the time since injection, when applicable, should be taken into account.

Many drugs used during the conduct of anesthesia are considered potential triggering agents for familial malignant hyperthermia. Because it is not known whether amide-type local anesthetics may trigger this reaction and because the need for supplemental general anesthesia cannot be predicted in advance, it is suggested that a standard protocol for management should be available. Early unexplained signs of tachycardia, tachypnea, labile blood pressure, and metabolic acidosis may precede temperature elevation. Successful outcome is dependent on early diagnosis, prompt discontinuance of the suspect triggering agent(s) and institution of treatment, including oxygen therapy, indicated supportive measures, and dantrolene. (Consult dantrolene sodium intravenous package insert before using.)

The following conditions may preclude the use of spinal anesthesia, depending upon the physician’s evaluation of the situation and ability to deal with the complications or complaints which may occur:

- Pre-existing diseases of the central nervous system, such as those attributable to pernicious anemia, poliomyelitis, syphilis, or tumor.
- Hematological disorders predisposing to coagulopathies or patients on anticoagulant therapy. Trauma to a blood vessel during the conduct of spinal anesthesia may, in some instances, result in uncontrollable central nervous system hemorrhage or soft tissue hemorrhage.
- Chronic backache and preoperative headache.
- Hypotension and hypertension.
- Technical problems (persistent paresthesias, persistent bloody tap).
- Arthritis or spinal deformity.
- Extremes of age.
- Psychosis or other causes of poor cooperation by the patient.

Information for Patients: When appropriate, patients should be informed in advance that they may experience temporary loss of sensation and motor activity, usually in the lower half of the body, following proper administration of spinal anesthesia. Also, when appropriate, the physician should discuss other information including adverse reactions in the MARCAINE Spinal package insert.

Clinically Significant Drug Interactions: The administration of local anesthetic solutions containing epinephrine or norepinephrine to patients receiving monoamine oxidase inhibitors or tricyclic antidepressants may produce severe, prolonged hypertension. Concurrent use of these agents should generally be avoided. In situations when concurrent therapy is necessary, careful patient monitoring is essential.

Concurrent administration of vasopressor drugs and of ergot-type oxytocic drugs may cause severe persistent hypertension or cerebrovascular accidents.

Phenothiazines and butyrophenones may reduce or reverse the pressor effect of epinephrine.

Carcinogenesis, Mutagenesis, and Impairment of Fertility: Long-term studies in animals to evaluate the carcinogenic potential of bupivacaine hydrochloride have not been conducted. The mutagenic potential and the effect on fertility of bupivacaine hydrochloride have not been determined.

PREGNANCY

Pregnancy Category C: Decreased pup survival in rats and an embryocidal effect in rabbits have been observed when bupivacaine hydrochloride was administered to these species in doses comparable to 230 and 130 times respectively the maximum recommended human spinal dose. There are no adequate and well-controlled studies in pregnant women of the effect of bupivacaine on the developing fetus. Bupivacaine hydrochloride should be used during pregnancy only if the potential benefit justifies the potential risk to the fetus. This does not exclude the use of MARCAINE Spinal at term for obstetrical anesthesia. (See Labor and Delivery.)

Labor and Delivery: Spinal anesthesia has a recognized use during labor and delivery. Bupivacaine hydrochloride, when administered properly, via the epidural route in doses 10 to 12 times the amount used in spinal anesthesia has been used for obstetrical analgesia and anesthesia without evidence of adverse effects on the fetus.

Maternal hypotension has resulted from regional anesthesia. Local anesthetics produce vasodilation by blocking sympathetic nerves. Elevating the patient’s legs and positioning her on her left side will help prevent decreases in blood pressure. The fetal heart rate also should be monitored continuously and electronic fetal monitoring is highly advisable.

It is extremely important to avoid aortocaval compression by the gravid uterus during administrations of regional block to parturients. To do this, the patient must be maintained in the left lateral decubitus position or a blanket roll or sandbag may be placed beneath the right hip and the gravid uterus displaced to the left.

Spinal anesthesia may alter the forces of parturition through changes in uterine contractility or maternal expulsive efforts. Spinal anesthesia has also been reported to prolong the second stage of labor by removing the parturient’s reflex urge to bear down or by interfering with motor function. The use of obstetrical anesthesia may increase the need for forceps assistance.

The use of some local anesthetic drug products during labor and delivery may be followed by diminished muscle strength and tone for the first day or two of life. This has not been reported with bupivacaine.

There have been reports of cardiac arrest during use of MARCAINE 0.75% solution for epidural anesthesia in obstetrical patients. The package insert for MARCAINE hydrochloride for epidural, nerve block, etc., has a more complete discussion of preparation for, and management of, this problem. These cases are compatible with systemic toxicity following unintended intravascular injection of the much larger doses recommended for epidural anesthesia and have not occurred within the dose range of bupivacaine hydrochloride 0.75% recommended for spinal anesthesia in obstetrics. The 0.75% concentration of MARCAINE is therefore not recommended for obstetrical epidural anesthesia. MARCAINE Spinal (bupivacaine hydrochloride in dextrose injection) is recommended for spinal anesthesia in obstetrics.

Nursing Mothers: Bupivacaine has been reported to be excreted in human milk suggesting that the nursing infant could be theoretically exposed to a dose of the drug. Because of the potential for serious adverse reactions in nursing infants from bupivacaine, a decision should be made whether to discontinue nursing or not administer bupivacaine, taking into account the importance of the drug to the mother.

Pediatric Use: Until further experience is gained in patients younger than 18 years, administration of MARCAINE Spinal in this age group is not recommended.

Geriatric Use: Patients over 65 years, particularly those with hypertension, may be at increased risk for developing hypotension while undergoing spinal anesthesia with MARCAINE Spinal. (See PRECAUTIONS, General and ADVERSE REACTIONS, Cardiovascular System.)

Elderly patients may require lower doses of MARCAINE Spinal. (See PRECAUTIONS, General and DOSAGE AND ADMINISTRATION.)

In clinical studies, differences in various pharmacokinetic parameters have been observed between elderly and younger patients. (See CLINICAL PHARMACOLOGY, Pharmacokinetics.)

This product is known to be substantially excreted by the kidney, and the risk of toxic reactions to this drug may be greater in patients with impaired renal function. Because elderly patients are more likely to have decreased renal function, care should be taken in dose selection, and it may be useful to monitor renal function. (See CLINICAL PHARMACOLOGY, Pharmacokinetics.)

<paragraph>ADVERSE REACTIONS

Reactions to bupivacaine are characteristic of those associated with other amide-type local anesthetics.

The most commonly encountered acute adverse experiences which demand immediate countermeasures following the administration of spinal anesthesia are hypotension due to loss of sympathetic tone and respiratory paralysis or underventilation due to cephalad extension of the motor level of anesthesia. These may lead to cardiac arrest if untreated. In addition, dose-related convulsions and cardiovascular collapse may result from diminished tolerance, rapid absorption from the injection site, or from unintentional intravascular injection of a local anesthetic solution. Factors influencing plasma protein binding, such as acidosis, systemic diseases which alter protein production, or competition of other drugs for protein binding sites, may diminish individual tolerance.

Respiratory System: Respiratory paralysis or underventilation may be noted as a result of upward extension of the level of spinal anesthesia and may lead to secondary hypoxic cardiac arrest if untreated. Preanesthetic medication, intraoperative analgesics and sedatives, as well as surgical manipulation, may contribute to underventilation. This will usually be noted within minutes of the injection of spinal anesthetic solution, but because of differing maximal onset times, differing intercurrent drug usage and differing surgical manipulation, it may occur at any time during surgery or the immediate recovery period.

Cardiovascular System: Hypotension due to loss of sympathetic tone is a commonly encountered extension of the clinical pharmacology of spinal anesthesia. This is more commonly observed in elderly patients, particularly those with hypertension, and patients with shrunken blood volume, shrunken interstitial fluid volume, cephalad spread of the local anesthetic, and/or mechanical obstruction of venous return. Nausea and vomiting are frequently associated with hypotensive episodes following the administration of spinal anesthesia. High doses, or inadvertent intravascular injection, may lead to high plasma levels and related depression of the myocardium, decreased cardiac output, bradycardia, heart block, ventricular arrhythmias, and, possibly, cardiac arrest. (See WARNINGS, PRECAUTIONS, and OVERDOSAGE sections.)

Central Nervous System: Respiratory paralysis or underventilation secondary to cephalad spread of the level of spinal anesthesia (see Respiratory System) and hypotension for the same reason (see Cardiovascular System) are the two most commonly encountered central nervous system-related adverse observations which demand immediate countermeasures.

High doses or inadvertent intravascular injection may lead to high plasma levels and related central nervous system toxicity characterized by excitement and/or depression. Restlessness, anxiety, dizziness, tinnitus, blurred vision, or tremors may occur, possibly proceeding to convulsions. However, excitement may be transient or absent, with depression being the first manifestation of an adverse reaction. This may quickly be followed by drowsiness merging into unconsciousness and respiratory arrest.

Neurologic: The incidences of adverse neurologic reactions associated with the use of local anesthetics may be related to the total dose of local anesthetic administered and are also dependent upon the particular drug used, the route of administration, and the physical status of the patient. Many of these effects may be related to local anesthetic techniques, with or without a contribution from the drug.

Neurologic effects following spinal anesthesia may include loss of perineal sensation and sexual function; persistent anesthesia, paresthesia, weakness and paralysis of the lower extremities, and loss of sphincter control all of which may have slow, incomplete, or no recovery; hypotension, high or total spinal block; urinary retention; headache; backache; septic meningitis, meningismus; arachnoiditis; slowing of labor; increased incidence of forceps delivery; shivering; cranial nerve palsies due to traction on nerves from loss of cerebrospinal fluid; and fecal and urinary incontinence.

Allergic: Allergic-type reactions are rare and may occur as a result of sensitivity to the local anesthetic. These reactions are characterized by signs such as urticaria, pruritus, erythema, angioneurotic edema (including laryngeal edema), tachycardia, sneezing, nausea, vomiting, dizziness, syncope, excessive sweating, elevated temperature, and, possibly, anaphylactoid-like symptomatology (including severe hypotension). Cross sensitivity among members of the amide-type local anesthetic group has been reported. The usefulness of screening for sensitivity has not been definitely established.

Other: Nausea and vomiting may occur during spinal anesthesia.

<paragraph>OVERDOSAGE

Acute emergencies from local anesthetics are generally related to high plasma levels encountered during therapeutic use or to underventilation (and perhaps apnea) secondary to upward extension of spinal anesthesia. Hypotension is commonly encountered during the conduct of spinal anesthesia due to relaxation of sympathetic tone, and sometimes, contributory mechanical obstruction of venous return.

Management of Local Anesthetic Emergencies: The first consideration is prevention, best accomplished by careful and constant monitoring of cardiovascular and respiratory vital signs and the patient’s state of consciousness after each local anesthetic injection. At the first sign of change, oxygen should be administered.

The first step in the management of systemic toxic reactions, as well as underventilation or apnea due to a high or total spinal, consists of immediate attention to the establishment and maintenance of a patent airway and effective assisted or controlled ventilation with 100% oxygen with a delivery system capable of permitting immediate positive airway pressure by mask. This may prevent convulsions if they have not already occurred.

If necessary, use drugs to control the convulsions. A 50 mg to 100 mg bolus IV injection of succinylcholine will paralyze the patient without depressing the central nervous or cardiovascular systems and facilitate ventilation. A bolus IV dose of 5 mg to 10 mg of diazepam or 50 mg to 100 mg of thiopental will permit ventilation and counteract central nervous system stimulation, but these drugs also depress central nervous system, respiratory and cardiac function, add to postictal depression and may result in apnea. Intravenous barbiturates, anticonvulsant agents, or muscle relaxants should only be administered by those familiar with their use. Immediately after the institution of these ventilatory measures, the adequacy of the circulation should be evaluated. Supportive treatment of circulatory depression may require administration of intravenous fluids, and, when appropriate, a vasopressor dictated by the clinical situation (such as ephedrine or epinephrine to enhance myocardial contractile force).

Hypotension due to sympathetic relaxation may be managed by giving intravenous fluids (such as isotonic saline or lactated Ringer’s solution), in an attempt to relieve mechanical obstruction of venous return, or by using vasopressors (such as ephedrine which increases the force of myocardial contractions) and, if indicated, by giving plasma expanders or whole blood.

Endotracheal intubation, employing drugs and techniques familiar to the clinician, may be indicated after initial administration of oxygen by mask if difficulty is encountered in the maintenance of a patent airway, or if prolonged ventilatory support (assisted or controlled) is indicated.

Recent clinical data from patients experiencing local anesthetic-induced convulsions demonstrated rapid development of hypoxia, hypercarbia, and acidosis with bupivacaine within a minute of the onset of convulsions. These observations suggest that oxygen consumption and carbon dioxide production are greatly increased during local anesthetic convulsions and emphasize the importance of immediate and effective ventilation with oxygen which may avoid cardiac arrest.

If not treated immediately, convulsions with simultaneous hypoxia, hypercarbia, and acidosis plus myocardial depression from the direct effects of the local anesthetic may result in cardiac arrhythmias, bradycardia, asystole, ventricular fibrillation, or cardiac arrest. Respiratory abnormalities, including apnea, may occur. Underventilation or apnea due to a high or total spinal may produce these same signs and also lead to cardiac arrest if ventilatory support is not instituted. If cardiac arrest should occur, standard cardiopulmonary resuscitative measures should be instituted and maintained for a prolonged period if necessary. Recovery has been reported after prolonged resuscitative efforts.

The supine position is dangerous in pregnant women at term because of aortocaval compression by the gravid uterus. Therefore during treatment of systemic toxicity, maternal hypotension, or fetal bradycardia following regional block, the parturient should be maintained in the left lateral decubitus position if possible, or manual displacement of the uterus off the great vessels be accomplished.

The mean seizure dosage of bupivacaine in rhesus monkeys was found to be 4.4 mg/kg with mean arterial plasma concentration of 4.5 mcg/mL. The intravenous and subcutaneous LD50 in mice is 6 mg/kg to 8 mg/kg and 38 mg/kg to 54 mg/kg respectively.

<paragraph>DOSAGE AND ADMINISTRATION

The dose of any local anesthetic administered varies with the anesthetic procedure, the area to be anesthetized, the vascularity of the tissues, the number of neuronal segments to be blocked, the depth of anesthesia and degree of muscle relaxation required, the duration of anesthesia desired, individual tolerance, and the physical condition of the patient. The smallest dose and concentration required to produce the desired result should be administered. Dosages of MARCAINE Spinal should be reduced for elderly and debilitated patients and patients with cardiac and/or liver disease.

For specific techniques and procedures, refer to standard textbooks.

There have been adverse event reports of chondrolysis in patients receiving intra-articular infusions of local anesthetics following arthroscopic and other surgical procedures. MARCAINE Spinal is not approved for this use (see WARNINGS and DOSAGE AND ADMINISTRATION).

The extent and degree of spinal anesthesia depend upon several factors including dosage, specific gravity of the anesthetic solution, volume of solution used, force of injection, level of puncture, and position of the patient during and immediately after injection.

Seven and one-half mg (7.5 mg or 1 mL) MARCAINE Spinal has generally proven satisfactory for spinal anesthesia for lower extremity and perineal procedures including TURP and vaginal hysterectomy. Twelve mg (12 mg or 1.6 mL) has been used for lower abdominal procedures such as abdominal hysterectomy, tubal ligation, and appendectomy. These doses are recommended as a guide for use in the average adult and may be reduced for the elderly or debilitated patients. Because experience with MARCAINE Spinal is limited in patients below the age of 18 years, dosage recommendations in this age group cannot be made.

Obstetrical Use: Doses as low as 6 mg bupivacaine hydrochloride have been used for vaginal delivery under spinal anesthesia. The dose range of 7.5 mg to 10.5 mg (1 mL to 1.4 mL) bupivacaine hydrochloride has been used for Cesarean section under spinal anesthesia.

In recommended doses, MARCAINE Spinal produces complete motor and sensory block.

Unused portions of solutions should be discarded following initial use.

MARCAINE Spinal should be inspected visually for discoloration and particulate matter prior to administration; solutions which are discolored or which contain particulate matter should not be administered.

<paragraph>HOW SUPPLIED

Single-dose ampuls of 2 mL (15 mg bupivacaine hydrochloride with 165 mg dextrose), is supplied as follows:

NDC No. | Container | Fill | Quantity
0409-1761-02 | Uni-AmpTM | 2 mL | package of 10
0409-1761-62 | Uni-AmpTM | 2 mL | bulk package of 800

Store at 20 to 25ºC (68 to 77ºF). [See USP Controlled Room Temperature.]

MARCAINE Spinal solution may be autoclaved once at 15 pound pressure, 121°C (250°F) for 15 minutes. Do not administer any solution which is discolored or contains particulate matter.

Hospira, Inc., Lake Forest, IL 60045 USA

Package Label Display Panel

Epinephrine Pack Label

Lidocaine Pack Label

PACKAGE LABEL

<paragraph>
3/4 Fluid Ounce Povidone Iodine

Povidone-iodine 10%

Antiseptic

Warnings

Do not use

- if allergic to iodine
- in the eyes

For external use only

Ask a doctor before use if injuries are

- deep or puncture wounds
- serious burns

Stop use and ask a doctor if

- redness, irritation, swelling or pain persists or increases
- infection occurs

Avoid pooling beneath patient

Keep out of reach of children.In case of accidental ingestion, seek professional assistance or consult a poison control center immediately.